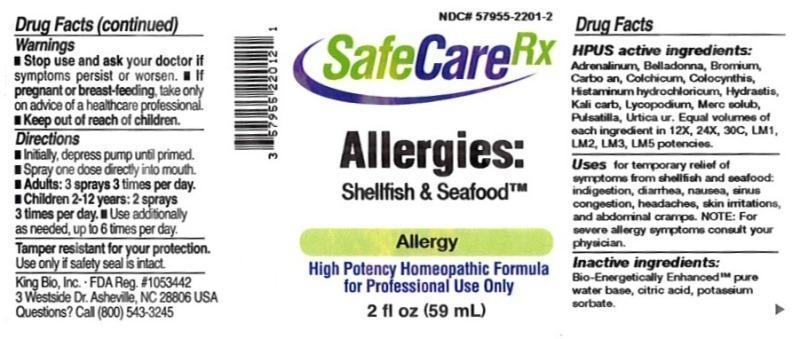 DRUG LABEL: Allergies Shellfish and Seafood
NDC: 57955-2201 | Form: LIQUID
Manufacturer: King Bio Inc.
Category: homeopathic | Type: HUMAN OTC DRUG LABEL
Date: 20150728

ACTIVE INGREDIENTS: EPINEPHRINE 12 [hp_X]/59 mL; ATROPA BELLADONNA 12 [hp_X]/59 mL; BROMINE 12 [hp_X]/59 mL; CARBO ANIMALIS 12 [hp_X]/59 mL; COLCHICUM AUTUMNALE BULB 12 [hp_X]/59 mL; CITRULLUS COLOCYNTHIS FRUIT PULP 12 [hp_X]/59 mL; HISTAMINE DIHYDROCHLORIDE 12 [hp_X]/59 mL; GOLDENSEAL 12 [hp_X]/59 mL; POTASSIUM CARBONATE 12 [hp_X]/59 mL; LYCOPODIUM CLAVATUM SPORE 12 [hp_X]/59 mL; MERCURIUS SOLUBILIS 12 [hp_X]/59 mL; PULSATILLA VULGARIS 12 [hp_X]/59 mL; URTICA URENS 12 [hp_X]/59 mL
INACTIVE INGREDIENTS: WATER; POTASSIUM SORBATE; ANHYDROUS CITRIC ACID

Allergies: Shellfish and Seafood

ACTIVE INGREDIENT

Drug Facts__________________________________________________________________________________________________________

HPUS active ingredients: Adrenalinum. Belladonna, Bromium, Carbo animalis, Colchicum autumnale, Colocynthis, Histaminum hydrochloricum, Hydrastis canadensis, Kali carbonicum, Lycopodium clavatum, Mercurius solubilis, Pulsatilla, Urtica urens. Equal volumes of each ingredient in 12X, 24X, 30C, LM1, LM2, LM3, LM5 potencies.

INDICATIONS AND USAGE

Uses for temporary relief of symptoms from shellfish and seafood: indigestion, diarrhea, nausea, sinus congestion, headaches, skin irritations, and abdominal cramps. Note: For severe allergy symptoms consult your physician.

Inactive Ingredients:

Bio-Energetically Enhanced™ pure water, citric acid and potassium sorbate.

Warnings

- Stop use and ask your doctor if symptoms persist or worsen.
- If pregnant or breast-feeding, take only on advice of a healthcare professional.

- Keep out of reach of children.

Directions

- Initially, depress pump until primed.
- Spray one dose directly into mouth.
- Adults: 3 sprays 3 times per day.
- Children 2-12: 2 sprays 3 times per day.
- Use additionally as needed, up to 6 times per day.

OTHER SAFETY INFORMATION

Tamper resistant for your protection. Use only if seal is intact.

PURPOSE

Uses for temporary relief of symptoms from shellfish and seafood:

- indigestion
- diarrhea
- nausea
- sinus
- congestion
- headaches
- skin irritations
- abdominal cramps
- Note: For severe allergy symptoms consult your physician.